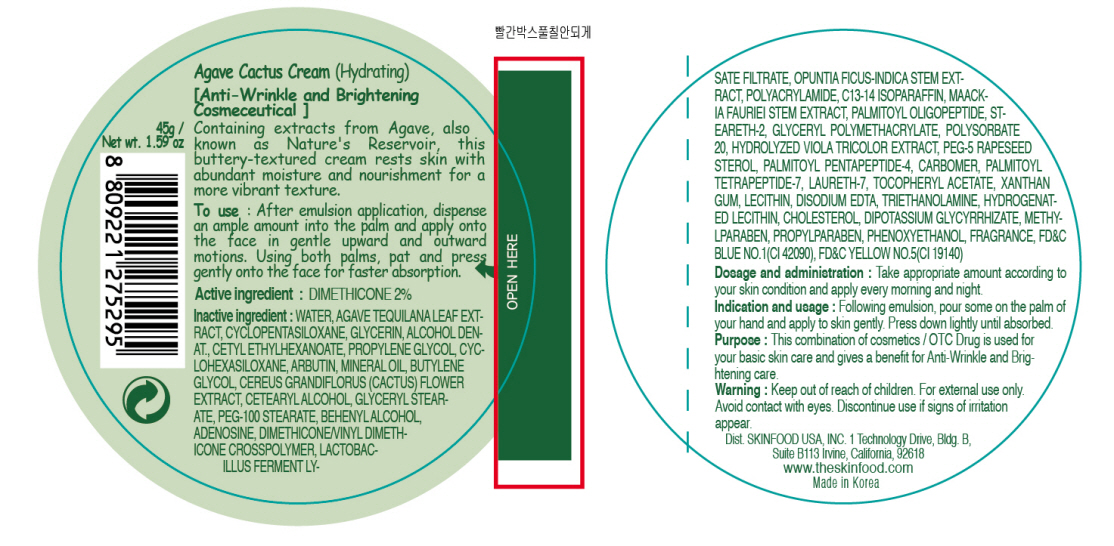 DRUG LABEL: AGAVE CACTUS
NDC: 76214-006 | Form: CREAM
Manufacturer: SKINFOOD CO., LTD.
Category: otc | Type: HUMAN OTC DRUG LABEL
Date: 20110722

ACTIVE INGREDIENTS: DIMETHICONE 0.9 g/45 g
INACTIVE INGREDIENTS: WATER; AGAVE TEQUILANA LEAF; CYCLOMETHICONE 5; GLYCERIN; CETYL ETHYLHEXANOATE; CYCLOMETHICONE 6; PROPYLENE GLYCOL; ARBUTIN; MINERAL OIL; BUTYLENE GLYCOL; CETOSTEARYL ALCOHOL; PEG-100 STEARATE; GLYCERYL MONOSTEARATE; DOCOSANOL; LECITHIN, SOYBEAN; OPUNTIA FICUS-INDICA STEM; PHENOXYETHANOL; METHYLPARABEN; C13-14 ISOPARAFFIN; MAACKIA FLORIBUNDA STEM; PALMITOYL OLIGOPEPTIDE; STEARETH-2; POLYSORBATE 20; PROPYLPARABEN; PALMITOYL PENTAPEPTIDE-4; PALMITOYL TETRAPEPTIDE-7; LAURETH-7; XANTHAN GUM; ADENOSINE; TROLAMINE; EDETATE DISODIUM; HYDROGENATED SOYBEAN LECITHIN; CHOLESTEROL

Drug Facts

Active ingredient: DIMETHICONE

Inactive ingredients:

WATER, AGAVE TEQUILANA LEAF EXTRACT, CYCLOPENTASILOXANE, GLYCERIN, ALCOHOL DENAT., CETYL ETHYLHEXANOATE, CYCLOHEXASILOXANE, PROPYLENE GLYCOL, ARBUTIN, MINERAL OIL, BUTYLENE GLYCOL, CEREUS GRANDIFLORUS (CACTUS) FLOWER EXTRACT, CETEARYL ALCOHOL, GLYCERYL STEARATE, PEG-100 STEARATE, BEHENYL ALCOHOL, ADENOSINE, DIMETHICONE/VINYL DIMETHICONE CROSSPOLYMER, LACTOBACILLUS FERMENT LYSATE FILTRATE, OPUNTIA FICUS-INDICA STEM EXTRACT, POLYACRYLAMIDE, C13-14 ISOPARAFFIN, MAACKIA FAURIEI STEM EXTRACT, PALMITOYL OLIGOPEPTIDE, STEARETH-2, GLYCERYL POLYMETHACRYLATE, POLYSORBATE 20, HYDROLYZED VIOLA TRICOLOR EXTRACT, PEG-5 RAPESEED STEROL, PALMITOYL PENTAPEPTIDE-4, CARBOMER, PALMITOYL TETRAPEPTIDE-7, LAURETH-7, TOCOPHERYL ACETATE, XANTHAN GUM, LECITHIN, DISODIUM EDTA, TRIETHANOLAMINE, HYDROGENATED LECITHIN, CHOLESTEROL, DIPOTASSIUM GLYCYRRHIZATE, METHYLPARABEN, PROPYLPARABEN, PHENOXYETHANOL, FRAGRANCE

Purpose:

This combination of cosmetics is used for your basic skin care and gives a benefit for Anti-Wrinkle and Brightening care.

Warnings:

For external use only. Avoid contact with eyes. Discontinue use if signs of irritation appear.

Keep out of reach of children:

Keep out of reach of children.

Indication and usage:

Following emulsion, pour some on the palm of your hand and apply to skin gently. Press down lightly until absorbed.

Dosage and administration:

Take appropriate amount according to your skin condition and apply every morning and night.